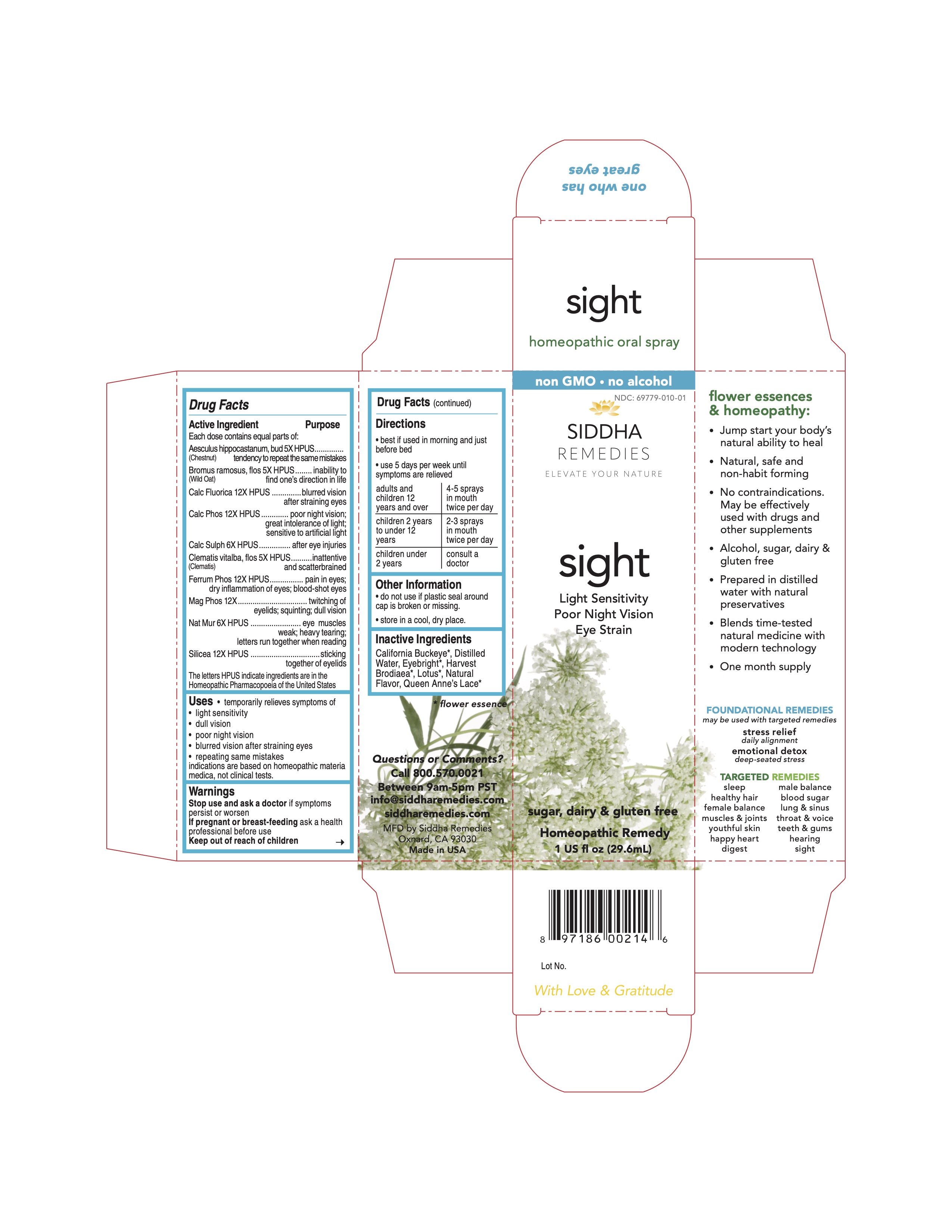 DRUG LABEL: sight
NDC: 69779-010 | Form: SPRAY
Manufacturer: Siddha Flower Essences LLC
Category: homeopathic | Type: HUMAN OTC DRUG LABEL
Date: 20251231

ACTIVE INGREDIENTS: HORSE CHESTNUT 5 [hp_X]/29.6 mL; BROMUS RAMOSUS FLOWER 5 [hp_X]/29.6 mL; CALCIUM FLUORIDE 12 [hp_X]/29.6 mL; TRIBASIC CALCIUM PHOSPHATE 12 [hp_X]/29.6 mL; CALCIUM SULFATE ANHYDROUS 6 [hp_X]/29.6 mL; CLEMATIS VITALBA FLOWER 5 [hp_X]/29.6 mL; FERROSOFERRIC PHOSPHATE 12 [hp_X]/29.6 mL; MAGNESIUM PHOSPHATE, DIBASIC TRIHYDRATE 12 [hp_X]/29.6 mL; SODIUM CHLORIDE 6 [hp_X]/29.6 mL; SILICON DIOXIDE 12 [hp_X]/29.6 mL
INACTIVE INGREDIENTS: WATER; NELUMBO NUCIFERA FLOWER

Drug Facts

Active Ingredient

Each dose contains equal parts of:

Aesculus hippocastanum, bud (Chestnut Bud) 5X HPUS

Bromus ramosus, flos (Wild Oat) 5X HPUS
Calc Fluorica 12X HPUS
Calc Phos 12X HPUS
Calc Sulph 6X HPUS
Clematis vitalba, flos (Clematis) 5X HPUS
Ferrum Phos 12X HPUS
Mag Phos 12X
Nat Mur 6X HPUS
Silicea 12X HPUS

Purpose

Each dose contains equal parts of:

Aesculus hippocastanum, bud (Chestnut Bud) 5X HPUS..........tendency to repeat the same mistakes
Bromus ramosus, flos (Wild Oat) 5X HPUS.............................inability to find one's direction in life
Calc Fluorica 12X HPUS........................................................blurred vision after straining eyes
Calc Phos 12X HPUS............................................................poor night vision; great intolerance of light; sensitive to artificial light
Calc Sulph 6X HPUS.............................................................after eye injuries
Clematis vitalba, flos (Clematis) 5X HPUS...............................inattentive and scatterbrained
Ferrum Phos 12X HPUS........................................................pain in eyes; dry inflammation of eyes; blood-shot eyes
Mag Phos 12X......................................................................twitching of eyelids; squinting; dull vision
Nat Mur 6X HPUS.................................................................eye muscles weak; heavy tearing; letters run together when reading
Silicea 12X HPUS.................................................................sticking together of eyelids
The letters HPUS indicate ingredients are in the Homeopathic Pharmacopoeia of the United States.

Uses

- temporarily relives symptoms of
- light sensitivity
- dull vision
- poor night vision
- blurred vision after straining eyes
- repeating same mistakes

indications are based on homeopathic materia medica, not clinical tests.

Warnings

Stop use and ask a doctor if symptoms persist or worsen

PREGNANCY OR BREAST FEEDING

If pregnant or breast-feeding ask a health professional before use

Keep out of reach of children

Directions

- best if used in morning and just before bed
- use 5 days per week until symptoms are relieved

adults and children 12 and over | 4-5 sprays in mouth twice per day
children 2 years to under 12 years | 2-3 sprays in mouth twice per day
children under 2 years | consult a doctor

Inactive Ingredients

California Buckeye*, Eyebright*, Harvest Brodiaea*, Lotus*, Natural Flavor, Purified Water, Queen Anne's Lace*

*flower essence

Questions or Comments?
Call 800.570.0021
Between 9am-5pm PST
info@siddhaflowers.com
siddhaflowers.com

MFD by Siddha Flower Essences
Oxnard, CA 93030

Made in USA

Side Panel

flower essences and homeopathy:

- Jump start your body's natural ability to heal
- Natural, safe and non-habit forming
- No contraindications. May be effectively used with drugs and other supplements
- Alcohol, sugar, dairy and gluten free
- Prepared in purified water with natural preservatives
- Blends time-tested natural medicine with modern technology
- One month supply

FOUNDATIONAL REMEDIES
may be used with targeted remedies

stress relief
daily alignment
emotional detox
deep-seated stress

TARGETED REMEDIES

sleep male balance
healthy hair blood sugar
female balance lung and sinus
muscles and joints throat and voice
youthful skin teeth and gums
happy heart hearing
digestion sight

Principal Display Panel

non GMO - no alcohol
siddha cell salts + flower essences
sight
Light Sensitivity
Poor Night Vision
Eye Strain
sugar, dairy and gluten free
Homeopathic Remedy
1 US fl oz (29.6mL)